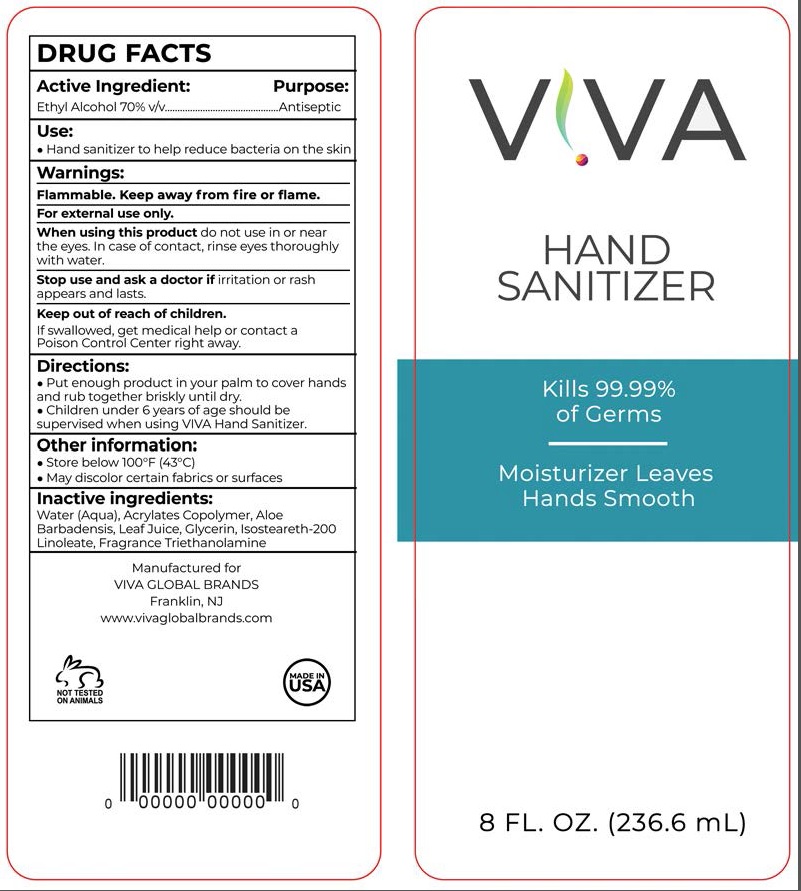 DRUG LABEL: VIVA
NDC: 76549-070 | Form: SOLUTION
Manufacturer: Viva Products
Category: otc | Type: HUMAN OTC DRUG LABEL
Date: 20200409

ACTIVE INGREDIENTS: ALCOHOL 70 mL/100 mL
INACTIVE INGREDIENTS: WATER; BUTYL ACRYLATE/METHYL METHACRYLATE/METHACRYLIC ACID COPOLYMER (18000 MW); ALOE VERA LEAF; GLYCERIN; TROLAMINE

Active Ingredient

Ethyl Alcohol 70% v/v.

Purpose

Antiseptic

Use

Hand Sanitizer to help reduce bacteria on the skin

Warnings

Flammable. Keep away from fire or flame. For external use only.

When using this product

do not use in or near the eyes. In case of contact, rinse eyes thoroughly with water.

Stop use and ask a doctor if

irritation or rash appears and lasts

Keep out of reach of children.

If swallowed, get medical help or contact a Poison Control Center right away.

Directions

- Put enough product in your palm to cover hands and rub hands together briskly until dry
- Children under 6 years of age should be supervised when using VIVA Hand sanitizer

Storage

- Store below 110°F (43°C)
- May discolor certain fabrics or surfaces

Inactive ingredients

Water (Aqua), Acrylates Copolymer, Aloe Barbadensis Leaf Juice, Glycerin, Isosteareth-200 Linoleate, Fragrance Triethanolamine

Principal Display Panel

NDC 76549-070-01, 76549-070-02, 76549-070-03, 76549-070-04, 76549-070-08, 76549-070-09, 76549-070-16, 76549-070-37

VIVA

HAND SANITIZER

KILLS 99.99% OF GERMS

Moisturizer Leaves Hands Smooth

1.7 FL OZ (50 mL)

2 FL OZ (60 mL)

3.4 FL OZ (100 mL)

4 FL OZ (118 mL)

8 FL OZ (236.6 mL)

8.5 FL OZ (251 mL)

16 FL OZ (473 mL)

1 Gallon (3785 mL)